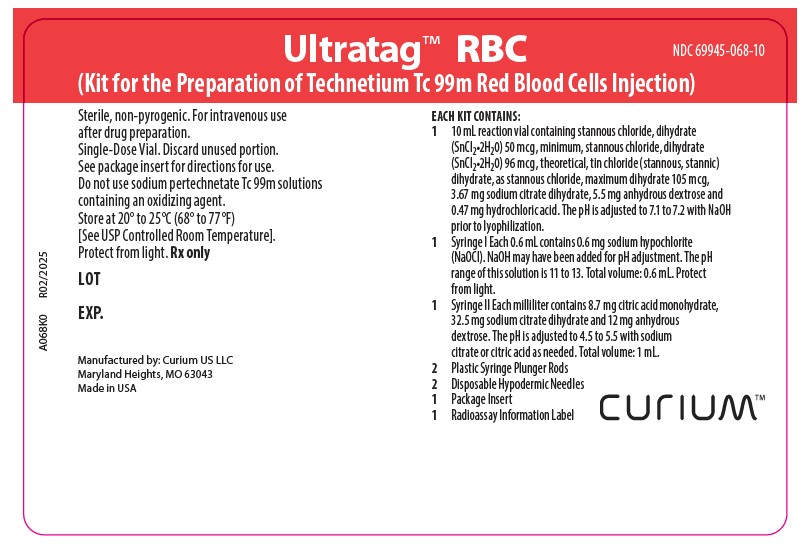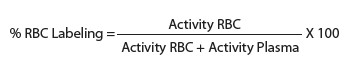 DRUG LABEL: Ultratag

NDC: 69945-068 | Form: KIT | Route: INTRAVENOUS
Manufacturer: Curium US LLC
Category: prescription | Type: HUMAN PRESCRIPTION DRUG LABEL
Date: 20250702

ACTIVE INGREDIENTS: STANNOUS CHLORIDE 0.05 mg/9.5 mg
INACTIVE INGREDIENTS: ANHYDROUS DEXTROSE; TRISODIUM CITRATE DIHYDRATE; SODIUM HYDROXIDE; SODIUM HYPOCHLORITE; WATER; SODIUM HYDROXIDE; CITRIC ACID MONOHYDRATE; TRISODIUM CITRATE DIHYDRATE; WATER; ANHYDROUS DEXTROSE

UltratagTM RBC
(Kit for the preparation of Technetium Tc 99m Red Blood Cells Injection)

Rx only

Diagnostic–For Intravenous Use

DESCRIPTION

Ultratag™RBC (Kit for the Preparation of Technetium Tc 99m Red Blood Cells Injection) is a sterile, nonpyrogenic, diagnostic kit for the in vitro preparation of Technetium Tc 99m Red Blood Cells Injection.

Each kit consists of three separate nonradioactive components:

1. A 10 milliliter reaction vial containing:

Stannous Chloride, Dihydrate (SnCl2•2H2O) – 50 mcg minimum

Stannous Chloride, Dihydrate (SnCl2•2H2O) – 96 mcg theoretical

Tin Chloride (Stannous and Stannic), Dihydrate (as SnCl2•2H2O) – 105 mcg maximum

Sodium Citrate, Dihydrate – 3.67 mg

Dextrose, Anhydrous – 5.5 mg

Hydrochloric Acid – 0.47 mg

Prior to lyophilization, the pH is adjusted to 7.1 to 7.2 with sodium hydroxide. The contents of the vial are lyophilized and stored under argon.

2. Syringe I contains:

Sodium Hypochlorite – 0.6 mg in Sterile Water for Injection

The total volume of this syringe is 0.6 mL. Sodium hydroxide may have been added for pH adjustment. The pH of this solution is 11 to 13. The syringe must be protected from light to prevent degradation of the light-sensitive sodium hypochlorite.

3. Syringe II contains:

Citric Acid, Monohydrate – 8.7 mg

Sodium Citrate, Dihydrate – 32.5 mg

Dextrose, Anhydrous – 12 mg in Sterile Water for Injection

The total volume of this syringe is 1 mL. The pH range of this solution is adjusted to 4.5 to 5.5 with sodium citrate or citric acid as needed.

PHYSICALCHARACTERISTICS

Technetium Tc 99m decays by isomeric transition with a physical half-life of 6.02 hours.^1 The principal photon that is useful for detection and imaging is listed in Table 1.

Table 1. Principal Radiation Emission Data^1

Radiation | Mean % / Disintegration | Energy (keV)
Gamma-2 | 89.07 | 140.5

The specific gamma ray constant for technetium Tc 99m is 0.78 R/mCi-hr at 1 cm. The first half-value thickness of lead (Pb) for technetium Tc 99m is 0.017 cm. A range of values for the relative attenuation of the radiation emitted by this radionuclide resulting from the interposition of various thicknesses of lead (Pb) is presented in Table 2. For example, the use of 0.25 cm of lead will decrease the external radiation exposure by a factor of about 1000.

Table 2. Radiation Attenuation by Lead Shielding

Shield Thickness (Pb) cm | Coefficient of Attenuation
0.017 | 0.5
0.08 | 10^-1
0.16 | 10^-2
0.25 | 10^-3
0.33 | 10^-4

To correct for physical decay of this radionuclide, the fractions that remain at selected intervals after the time of calibration are presented in Table 3.

^1 Kocher, David C., "Radioactive Decay Tables," DOE/TIC 11026, 108 (1981).

Table 3. Physical Decay Chart:
Technetium Tc 99m, Half-Life:6.02 Hours

Hours | Fraction Remaining | Hours | Fraction Remaining
0* | 1.000 | 7 | 0.447
1 | 0.891 | 8 | 0.398
2 | 0.794 | 9 | 0.355
3 | 0.708 | 10 | 0.316
4 | 0.631 | 11 | 0.282
5 | 0.562 | 12 | 0.251
6 | 0.501

*Calibration Time

CLINICAL PHARMACOLOGY

In vitro Tc 99m red blood cell labeling is accomplished by adding 1.0 to 3.0 milliliters of autologous whole blood, anticoagulated with heparin or Anticoagulant Citrate Dextrose Solution (ACD), to the reaction vial. A portion of the stannous ion in the reaction vial diffuses across the red blood cell membrane and accumulates intracellularly. The in vitro Tc 99m red blood cell labeling efficiency can decrease in the presence of excess ACD. Excess ACD apparently impairs the diffusion of stannous ion across the red blood cell membrane. Therefore, the ACD concentration used for blood collection should not exceed 0.15 mL ACD per mL of blood. Sodium hypochlorite is then added to the reaction vial to oxidize the extracellular stannous ion. Since the hypochlorite does not cross the red blood cell membrane, the oxidation of stannous ion is selective for the extracellular tin. A citric acid, sodium citrate and dextrose solution is then added to the reaction vial to sequester any residual extracellular stannous ion, rendering it more readily available for oxidation by sodium hypochlorite.

Radioactive labeling of the red blood cells is completed by addition of sodium pertechnetate Tc 99m to the oxidized reaction vial. The pertechnetate Tc 99m diffuses across the red blood cell membrane and is reduced by the intracellular stannous ion. The reduced technetium Tc 99m cannot diffuse out of the red blood cell. The red blood cell labeling is essentially complete within 20 minutes of sodium pertechnetate Tc 99m addition to the reaction vial. Red blood cell labeling efficiency of ≥95% is typically obtained using this in vitro labeling procedure. In vitro Tc 99m red blood cell labeling efficiency can decrease when excessive amounts of Tc 99 are allowed to accumulate in the sodium pertechnetate Tc 99m generator eluate; in this situation, efficiency decreases even further if excess (i.e. >0.15 mL per mL of blood) ACD buffer is used. Therefore, long Tc 99 in-growth times are to be avoided; the use of fresh (≤24 hour in-growth time) sodium pertechnetate Tc 99m generator eluate is recommended. After the labeling procedure is completed, the technetium Tc 99m red blood cells are then reinjected intravenously into the patient for gamma scintigraphic imaging.

Following intravenous injection, the technetium Tc 99m red blood cells distribute within the blood pool with an estimated volume of distribution of approximately 5.6% of bodyweight. The technetium Tc 99m is well retained in the blood pool with an estimated biological half-life of approximately 29 hours. Of the total technetium Tc 99m retained in the whole blood pool 24 hours after administration, 95% remains bound to the red blood cells. Approximately 25% of the injected dose is excreted in the urine in the first 24 hours.

INDICATIONS AND USAGE

Technetium Tc 99m red blood cells are used for blood pool imaging, including cardiac first pass and gated equilibrium imaging and for detection of sites of gastrointestinal bleeding.

CONTRAINDICATIONS

None known.

WARNINGS

None known.

PRECAUTIONS

General

The components of the kit are sterile and nonpyrogenic. It is essential that the user follow the directions carefully and adhere to strict aseptic procedures during preparation.

The contents of the kit are intended only for use in the preparation of technetium Tc 99m red blood cells and are NOT to be administered directly to the patient.

The contents of this kit are not radioactive. After sodium pertechnetate Tc 99m is added, however, adequate shielding of the final preparation must be maintained.

Technetium Tc 99m red blood cells must be handled with care to ensure minimum radiation exposure to the patient, consistent with proper patient management, and to ensure minimum radiation exposure to occupational workers.

The labeled red blood cells must be reinjected only into the patient from whom the blood was drawn.

Nuclear medicine procedures involving withdrawal and reinjection of blood have the potential for transmission of blood borne pathogens. Procedures should be implemented to avoid administration errors and viral contamination of personnel during blood product labeling. A system of checks similar to the ones used for administering blood transfusions should be routine.

Clinical trials were conducted with a variety of prescription and nonprescription medications and showed no significant effect on the in vitro labeling efficiency of Ultratag™RBC. Unlike stannous pyrophosphate red blood cell kits, heparinized patients (11) showed minimal interference with Ultratag™ RBC labeling efficiency (95% with heparin, 97% without heparin).

It is recommended that the labeled red blood cells be administered within 30 minutes of preparation or as soon as possible thereafter. A small study showed that technetium Tc 99m red blood cells prepared with Ultratag™ RBC have equivalent in vivo labeling efficiency when administered both immediately after preparation (5 patients studied) and at 6 hours after preparation (6 patients studied) with a 24-hour labeling efficiency averaging 97% for both groups.

Radiopharmaceuticals should be used only by physicians who are qualified by specific training in the safe use and handling of radionuclides and whose experience and training have been approved by the appropriate government agency authorized to license the use of radionuclides.

Carcinogenesis, Mutagenesis, Impairment of Fertility

No long term animal studies have been performed to evaluate carcinogenic or mutagenic potential or to determine the effects on male or female fertility.

Pregnancy

Animal reproduction studies have not been conducted with technetium Tc 99m red blood cells. It is also not known whether this drug can cause fetal harm when administered to a pregnant woman or can affect reproductive capacity. Technetium Tc 99m red blood cells should be administered to a pregnant woman only if clearly needed. Ideally, examinations using radiopharmaceuticals, especially those elective in nature, of a woman of childbearing capability should be performed during the first few (approximately 10) days following the onset of menses.

Nursing Mothers

Technetium Tc 99m is excreted in human milk during lactation. Therefore, formula feedings should be substituted for breast feeding.

Pediatric Use

Safety and efficacy in pediatric patients have not been established.

ADVERSE REACTIONS

None known.

DOSAGE AND ADMINISTRATION

The Instructions for Preparation must be carefully followed for preparing technetium Tc 99m red blood cells using Ultratag™ RBC.

The suggested dose range of technetium Tc 99m red blood cells in the average patient (70 kg) is 370 MBq (10 mCi) to 740 MBq (20 mCi).

The patient dose should be measured by a suitable radioactivity calibration system immediately prior to administration.

Parenteral drug products should be inspected visually for particulate matter and discoloration prior to administration, whenever solution and container permit. Aseptic procedures and a shielded syringe should be employed in preparing and withdrawing doses for administration to patients. The user should wear waterproof gloves during the administration procedure.

RADIATION DOSIMETRY

The estimated radiation doses to an average adult (70 Kg) from an intravenous injection of a maximum dose of 740 MBq (20 mCi) of technetium Tc 99m red blood cells are shown in Table 4.

These radiation absorbed dose values were calculated using the Medical Internal Radiation Dose (MIRD) Committee Schema.

Table 4. Absorbed Radiation Dose Estimates^2
For Ultratag™ RBC Technetium Tc 99m
Red Blood Cells Injection*

Organ | mGy/740 MBq | rads/20 mCi
Total Body | 3.0 | 0.30
Spleen | 22 | 2.2
Bladder Wall | 4.8 | 0.48
Testes | 2.2 | 0.22
Ovaries | 3.2 | 0.32
Blood | 8.0 | 0.80
Red Marrow | 3.0 | 0.30
Heart Wall | 20 | 2.0
Liver | 5.8 | 0.58
Bone Surfaces | 4.8 | 0.48

* Assumes non-resting state and biological half-life for all organs and whole body of 63.7 hours. The peak percent dose for heart chambers is 15.5%, for liver is 5.57%, spleen is 4.07% and for remainder of body is 74.8%. Assumes patient voids at 2.0 hour intervals.

^2 Dose estimates based on Phase I human biodistribution data generated at Brookhaven National Laboratories. Dose estimates were calculated at Oak Ridge Associated Universities, Oak Ridge, Tennessee.

HOW SUPPLIED

Catalog Number 068.

Ultratag™ RBC consists of three separate nonradioactive components:

1. A 10 milliliter reaction vial containing:

Stannous Chloride, Dihydrate (SnCl2•2H2O) – 50 mcg minimum

Stannous Chloride, Dihydrate (SnCl2•2H2O) – 96 mcg theoretical

Tin Chloride (Stannous and Stannic), Dihydrate (as SnCl2•2H2O) – 105 mcg maximum

Sodium Citrate, Dihydrate – 3.67 mg

Dextrose, Anhydrous – 5.5 mg

Hydrochloric Acid – 0.47 mg

Prior to lyophilization, the pH is adjusted to 7.1 to 7.2 with sodium hydroxide. The contents of the vial are lyophilized and stored under argon.

2. Syringe I contains:

Sodium Hypochlorite – 0.6 mg in Sterile Water for Injection

The total volume of this syringe is 0.6 mL. Sodium hydroxide may have been added for pH adjustment. The pH of this solution is 11 to 13. The syringe must be protected from light to prevent degradation of the light-sensitive sodium hypochlorite.

3. Syringe II contains:

Citric Acid, Monohydrate – 8.7 mg

Sodium Citrate, Dihydrate – 32.5 mg

Dextrose, Anhydrous – 12 mg in Sterile Water for Injection

The total volume of this syringe is 1 mL. The pH range of this solution is adjusted to 4.5 to 5.5 with sodium citrate or citric acid as needed.

Storage

The kit should be stored at 20° to 25°C (68° to 77°F) [See USP Controlled Room Temperature]. Syringe I should be protected from light if not stored in the kit tray.

INSTRUCTIONS FOR USE

Instructions for the Preparation of Technetium Tc 99m Red Blood Cells Injection Using UltratagTM RBC

1. Collect patient's blood sample (1.0 to 3.0 mL) using heparin or ACD as an anticoagulant. The amount of ACD should not exceed 0.15 mL of ACD per mL of blood. The recommended amount of heparin is 10-15 units per mL of blood. DO NOT USE EDTA OR OXALATE AS AN ANTICOAGULANT.

2. Using a large-bore (19 to 21 gauge) needle, transfer 1.0 to 3.0 mL of anticoagulated whole blood to the reaction vial and gently mix to dissolve the lyophilized material. Allow to react for five minutes.

3. Add contents of Syringe I, mix by gently inverting four to five times.

4. Add the contents of Syringe II to the reaction vial. Mix by gently inverting four to five times.

5. Place the vial in a lead shield fitted with a lead cap and having a minimum wall thickness of 1/8 inch. Add 370 to 3700 MBq (10 to 100 mCi) sodium pertechnetate Tc 99m (in a volume of up to 3 mL) to the reaction vial. The avoidance of long technetium Tc 99 in-growth times and the use of fresh sodium pertechnetate Tc 99m generator eluate is recommended.

6. Mix by gently inverting reaction vial four to five times. Allow to react for 20 minutes with occasional mixing.

7. Technetium Tc 99m red blood cells should be injected within 30 minutes of preparation or as soon as possible thereafter.

8. If desired, assay labeling efficiency immediately prior to injection. Typical labeling efficiency is greater than 95%.

9. Mix gently prior to withdrawal of patient dose. Aseptically transfer the technetium Tc 99m red blood cells to a syringe for administration to the patient. Use largest bore needle compatible with patient administration to prevent hemolysis.

10. Assay the Tc 99m red blood cell patient dose in a suitable calibrator and complete the radioassay information label. Affix the radioassay information label to the shield.

NOTES

1. The kit does not contain an anticoagulant. Therefore, a syringe treated with ACD or heparin must be used for drawing the patient's blood. The amount of ACD should not exceed 0.15 mL of ACD per mL of blood. The recommended amount of heparin is 10-15 units per mL of blood. Improperly anticoagulated blood will be unsuitable for reinjection.

2. If desired, the labeling yield determination can be carried out as follows:

Transfer 0.2 mL of the technetium Tc 99m red blood cells to a centrifuge tube containing 2 mL of 0.9% NaCl. Centrifuge for five minutes and carefully pipet off the diluted plasma. Measure the radioactivity in the plasma and red blood cells separately in a suitable counter. Calculate labeling efficiency as follows:

This reagent kit is approved for distribution to persons licensed by the U.S. Nuclear Regulatory Commission to use byproduct material identified in Section 10 CFR 35.200 or under an equivalent license of an Agreement state.

©2025 Curium US LLC. UltratagTM RBC, CuriumTM, and the Curium logo are trademarks of a Curium company.

Manufactured by: Curium US LLC
Maryland Heights, MO 63043

Made in USA

A068I0

R06/2025

CURIUMTM

PRINCIPAL DISPLAY PANEL

69945-068-10

Ultratag™ RBC
(Kit for the Preparation of Technetium Tc 99m Red Blood Cells Injection)

Sterile, non-pyrogenic. For intravenous use after drug preparation.

Single-Dose Vial. Discard unused portion.

See package insert for directions for use.
Do not use sodium pertechnetate Tc 99m solutions containing an oxidizing agent.
Store at 20° to 25°C (68° to 77°F) [See USP Controlled Room Temperature].
Protect from light. Rx only

LOT

EXP.

EACH KIT CONTAINS:

110 mL reaction vial containing stannous chloride, dihydrate (SnCl 2•2H20) 50 mcg, minimum, stannous chloride, dihydrate (SnCl 2•2H20) 96 mcg, theoretical, tin chloride (stannous, stannic) dihydrate, as stannous chloride, maximum dihydrate 105 mcg, 3.67 mg sodium citrate dihydrate, 5.5 mg anhydrous dextrose and 0.47 mg hydrochloric acid. The pH is adjusted to 7.1 to 7.2 with NaOH prior to lyophilization.
1Syringe I Each 0.6 mL contains 0.6 mg sodium hypochlorite (NaOCl). NaOH may have been added for pH adjustment. The pH range of this solution is 11 to 13. Total volume: 0.6 mL. Protect from light.
1Syringe II Each milliliter contains 8.7 mg citric acid monohydrate, 32.5 mg sodium citrate dihydrate and 12 mg anhydrous dextrose. The pH is adjusted to 4.5 to 5.5 with sodium citrate or citric acid as needed. Total volume: 1 mL.
2Plastic Syringe Plunger Rods
2Disposable Hypodermic Needles
1Package Insert
1Radioassay Information Label

Manufactured by: Curium US LLC
Maryland Heights, MO 63043
Made in USA

A068K0

R02/2025

CURIUMTM